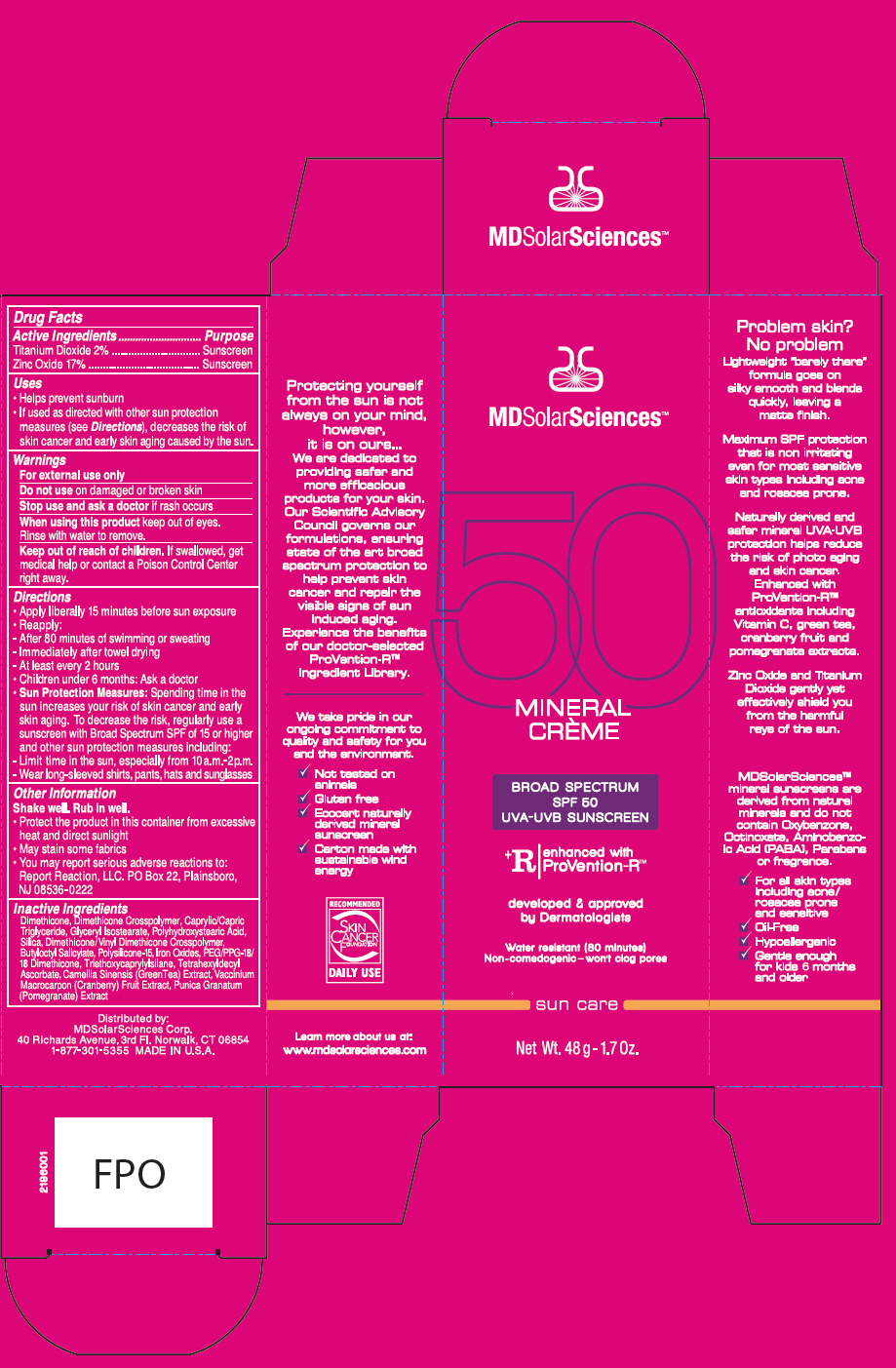 DRUG LABEL: Mineral 
NDC: 49358-554 | Form: CREAM
Manufacturer: MDSolarSciences
Category: otc | Type: HUMAN OTC DRUG LABEL
Date: 20180926

ACTIVE INGREDIENTS: Titanium Dioxide 2.7 g/35 g; Zinc Oxide 1.3 g/35 g
INACTIVE INGREDIENTS: Dimethicone; DIMETHICONE/DIENE DIMETHICONE CROSSPOLYMER; MEDIUM-CHAIN TRIGLYCERIDES; GLYCERYL ISOSTEARATE; POLYHYDROXYSTEARIC ACID (2300 MW); Silicon Dioxide; BUTYLOCTYL SALICYLATE; POLYSILICONE-15; DIMETHICONE/VINYL DIMETHICONE CROSSPOLYMER (SOFT PARTICLE); FERRIC OXIDE RED; PEG/PPG-18/18 DIMETHICONE; TRIETHOXYCAPRYLYLSILANE; TETRAHEXYLDECYL ASCORBATE; GREEN TEA LEAF; CRANBERRY; POMEGRANATE JUICE

Mineral Crème
Broad Spectrum SPF 50 Sunscreen UVA-UVB Suncreen

Drug Facts

ACTIVE INGREDIENT

Active Ingredients | Purpose
Titanium Dioxide 1.5% | Sunscreen
Zinc Oxide 17% | Sunscreen

Uses

- Helps prevent sunburn
- If used as directed with other sun protection measures (see Directions), decreases the risk of skin cancer and early skin aging caused by the sun.

Warnings

For external use only

Do not use on damaged or broken skin

Stop use and ask a doctor if rash occurs

When using this product keep out of eyes. Rinse with water to remove

Keep out of reach of children. If swallowed, get medical help or contact a Poison Control Center right away.

Directions

Shake well. Rub in well.

- Apply liberally 15 minutes before sun exposure
- Reapply:
  - After 80 minutes of swimming or sweating
  - Immediately after towel drying
  - At least every 2 hours
  - Children under 6 months: Ask a doctor
- Sun Protection Measures: Spending time in the sun increases your risk of skin cancer and early skin aging. To decrease the risk, regularly use a sunscreen with Broad Spectrum SPF of 15 or higher and other sun protection measures including:
  - Limit time in the sun, especially from 10a.m. – 2p.m.
  - Wear long-sleeved shirts, pants, hats and sunglasses

Other Information

- Protect the product in this container from excessive heat and direct sunlight
- May stain some fabrics
- You may report serious adverse reactions to: Report Reaction, LLC. PO Box 22, Plainsboro, NJ 08536-0222

Inactive ingredients

Dimethicone, Dimethicone Crosspolymer, Caprylic/Capric Triglyceride, Glyceryl Isostearate, Polyhydroxystearic Acid, Silica, Butyloctyl Salicylate, Polysilicone-15, Dimethicone/Vinyl Dimethicone Crosspolymer, Iron Oxides, PEG/PPG-18/18 Dimethicone, Triethoxycaprylylsilane, Tetrahexyldecyl Ascorbate, Camellia Sinensis (GreenTea) Extract, Vaccinium Macrocarpon (Cranbery) Fruit Extract, Punica Granatum (Pomegranate) Extract

PRINCIPAL DISPLAY PANEL - 48 g Tube Carton

MDSolarSciences™

50

MINERAL
CRÈME

BROAD SPECTRUM
SPF 50
UVA-UVB SUNSCREEN

^+R
enhanced with
ProVention-R™

developed & approved
by Dermatologists

Water resistant (80 minutes)
Non-comedogenic – won't clog pores

sun care

Net Wt. 48 g - 1.7 Oz